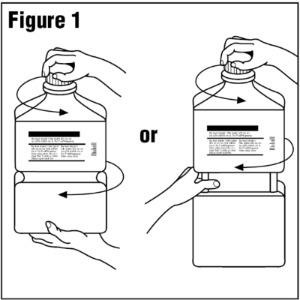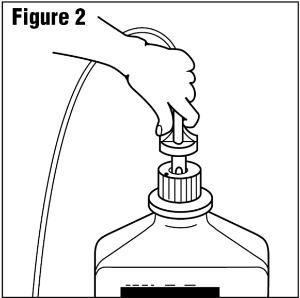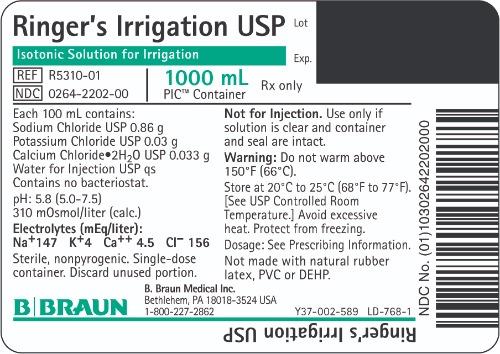 DRUG LABEL: Ringers
NDC: 0264-2202 | Form: IRRIGANT
Manufacturer: B. Braun Medical Inc.
Category: prescription | Type: HUMAN PRESCRIPTION DRUG LABEL
Date: 20230830

ACTIVE INGREDIENTS: SODIUM CHLORIDE 0.86 g/100 mL; POTASSIUM CHLORIDE 0.03 g/100 mL; CALCIUM CHLORIDE 0.033 g/100 mL
INACTIVE INGREDIENTS: WATER

Ringer's Irrigation USP

Package Insert

PIC™ (Plastic Irrigation Containers)

Ringer’s Irrigation USP

FOR ALL GENERAL IRRIGATION, WASHING AND RINSING PURPOSES

Not For Injection By Usual Parenteral Routes

Semi-rigid Irrigation Container

Rx only

DESCRIPTION

Ringer’s Irrigation USP is a sterile, nonpyrogenic, solution of electrolytes in water for injection intended only for sterile irrigation, washing and rinsing purposes.

Each 100 mL contains:

Sodium Chloride USP 0.86 g; Potassium Chloride USP 0.03 g
Calcium Chloride Dihydrate USP 0.033 g; Water for Injection USP qs

pH: 5.8 (5.0-7.5). The solution is isotonic (310 mOsmol/liter, calc.) and has the following electrolyte content (mEq/liter): Na^+ 147; K^+ 4 Ca^++ 4.5; Cl^− 156

The solution contains no bacteriostat, antimicrobial agent or added buffer and is intended only for use as a single-dose or short procedure irrigation. When smaller volumes are required the unused portion should be discarded. Ringer’s Irrigation USP may be classified as a sterile irrigant, wash, rinse and pharmaceutical vehicle.

The formulas of the active ingredients are:

Ingredients | Molecular Formula | Molecular Weight
Sodium Chloride USP | NaCl | 58.44
Potassium Chloride USP | KCl | 74.55
Calcium Chloride Dihydrate USP | CaCl2•2H2O | 147.01

The plastic container is a copolymer of ethylene and propylene formulated and developed for parenteral drugs. The copolymer contains no plasticizers and exhibits virtually no leachability. The plastic container is also virtually impermeable to vapor transmission and therefore, requires no overwrap to maintain the proper drug concentration. The safety of the plastic container has been confirmed by biological evaluation procedures. The material passes Class Vl testing as specified in the U.S. Pharmacopeia for Biological Tests — Plastic Containers. These tests have shown that the container is nontoxic and biologically inert.

Not made with natural rubber latex, PVC or DEHP.

CLINICAL PHARMACOLOGY

Ringer’s Irrigation USP exerts a mechanical cleansing action for sterile irrigation of body cavities, tissues or wounds, indwelling urethral catheters and surgical drainage tubes, and for washing, rinsing or soaking surgical dressings, instruments and laboratory specimens. It also serves as a vehicle for drugs used for irrigation or other pharmaceutical preparations.

Ringer’s Irrigation USP provides an isotonic irrigation with the same ionic constituents as Ringer’s Injection USP, a modification of Ringer’s solution (also called Ringer’s mixture) originally used only as a topical physiologic salt solution.

Ringer’s Irrigation USP is considered generally compatible with living tissues and organs. Calcium Chloride in water dissociates to provide calcium (Ca^++) and chloride (Cl^−) ions. They are normal constituents of the body fluids and are dependent on various physiologic mechanisms for maintenance of balance between intake and output. Approximately 80% of body calcium is excreted in the feces as insoluble salts; urinary excretion accounts for the remaining 20%.

Potassium chloride in water dissociates to provide potassium (K^+) and chloride (Cl^−) ions. Potassium is the chief cation of body cells (160 mEq/liter of intracellular water). It is found in low concentration in plasma and extracellular fluids (3.5 to 5.0 mEq/liter in a healthy adult). Potassium plays an important role in electrolyte balance.

Normally about 80 to 90% of the potassium intake is excreted in the urine; the remainder in the stools and to a small extent, in the perspiration. The kidney does not conserve potassium well so that during fasting or in patients on a potassium free diet, potassium loss from the body continues resulting in potassium depletion.

Sodium chloride in water dissociates to provide sodium (Na^+) and chloride (Cl^−) ions. Sodium (Na^+) is the principal cation of the extracellular fluid and plays a large part in the therapy of fluid and electrolyte disturbances. Chloride (Cl^−) has an integral role in buffering action when oxygen and carbon dioxide exchange occurs in the red blood cells. The distribution and excretion of sodium (Na^+) and chloride (Cl^−) are largely under the control of the kidney which maintains a balance between intake and output.

Water is an essential constituent of all body tissues and accounts for approximately 70% of total body weight. Average normal adult daily requirement ranges from two to three liters (1.0 to 1.5 liters each for insensible water loss by perspiration and urine production).

Water balance is maintained by various regulatory mechanisms. Water distribution depends primarily on the concentration of electrolytes in the body compartments and sodium (Na^+) plays a major role in maintaining physiologic equilibrium.

INDICATIONS AND USAGE

Ringer’s Irrigation USP is indicated for all general irrigation, washing and rinsing purposes which permit use of a sterile, nonpyrogenic electrolyte solution.

CONTRAINDICATIONS

NOT FOR INJECTION BY USUAL PARENTERAL ROUTES.

An electrolyte solution should not be used for irrigation during electrosurgical procedures.

WARNINGS

FOR IRRIGATION ONLY. NOT FOR INJECTION.

Irrigating fluids have been demonstrated to enter the systemic circulation in relatively large volumes; thus this irrigation must be regarded as a systemic drug. Absorption of large amounts can cause fluid and/or solute overloading resulting in dilution of serum electrolyte concentrations, overhydration, congested states or pulmonary edema.

The risk of dilutional states is inversely proportional to the electrolyte concentrations of administered parenteral solutions. The risk of solute overload causing congested states with peripheral and pulmonary edema is directly proportional to the electrolyte concentrations of such solutions.

Do not warm above 150°F (66°C).

After opening container, its contents should be used promptly to minimize the possibility of bacterial growth or pyrogen formation.

Discard unused portion of irrigating solution since it contains no preservatives.

PRECAUTIONS

General

Do not use for irrigation that may result in absorption into the blood.

Caution should be observed when the solution is used for continuous irrigation or allowed to “dwell” inside body cavities because of possible absorption into the blood stream and the production of circulatory overload.

Aseptic technique is essential with the use of sterile solutions for irrigation of body cavities, wounds and urethral catheters or for wetting dressings that come in contact with body tissues.

When used as a “pour” irrigation, no part of the contents should be allowed to contact the surface below the outer protected thread area of the semi-rigid wide mouth container. When used for irrigation via irrigation equipment, the administration set should be attached promptly. Unused portions should be discarded and a fresh container of appropriate size used for the start-up of each cycle or repeat procedure. For repeated irrigations of urethral catheters, a separate container should be used for each patient.

Use only if solution is clear and container and seal are intact. Discard unused portion.

Drug Interactions

Additives may be incompatible. Consult with pharmacist, if available. When introducing additives, use aseptic technique, mix thoroughly and do not store.

Carcinogenesis, Mutagenesis, Impairment of Fertility

Studies with Ringer’s Irrigation USP have not been performed to evaluate carcinogenic potential, mutagenic potential, or effects on fertility.

Pregnancy

Teratogenic Effects

Animal reproduction studies have not been conducted with Ringer’s Irrigation USP. It is also not known whether Ringer’s Irrigation USP can cause fetal harm when administered to a pregnant woman or can affect reproduction capacity. Ringer’s Irrigation USP should be given to a pregnant woman only if clearly needed.

Nursing Mothers

Caution should be exercised when Ringer’s Irrigation USP is administered to a nursing woman.

Pediatric Use

Safety and effectiveness in pediatric patients have not been established.

Geriatric Use

Clinical studies of Ringer’s Irrigation have not been performed to determine whether patients over 65 years respond differently from younger subjects. Other reported clinical experience has not identified differences in responses between elderly and younger patients. In general, dose selection for an elderly patient should be cautious, reflecting the greater frequency of decreased hepatic, renal, or cardiac function, and of concomitant disease or other drug therapy.

This drug is known to be substantially excreted by the kidney, and the risk of toxic reactions to this drug may be greater in patients with impaired renal function. Because elderly patients are more likely to have decreased renal function, care should be taken in dose selection, and it may be useful to monitor renal function.

ADVERSE REACTIONS

Possible adverse effects arising from the irrigation of body cavities, tissues, or indwelling catheters and tubes are usually avoidable when proper procedures are followed. Displaced catheters or drainage tubes can lead to irrigation or infiltration of unintended structures or cavities. Excessive volume or pressure during irrigation of closed cavities may cause undue distention or disruption of tissues. Accidental contamination from careless technique may transmit infection. Should any adverse reaction occur, discontinue the irrigant, evaluate the patient, institute appropriate therapeutic countermeasures and save the remainder of the fluid for examination if deemed necessary.

OVERDOSAGE

In the event of overhydration or solute overload, re-evaluate the patient and institute appropriate corrective measures. See WARNINGS, PRECAUTIONS, and ADVERSE REACTIONS.

DOSAGE AND ADMINISTRATION

The dose is dependent upon the capacity or surface area of the structure to be irrigated and the nature of the procedure. When used as a vehicle for other drugs, the manufacturer’s recommendations should be followed.

Parenteral drug products should be inspected visually for particulate matter and discoloration prior to administration, whenever solution and container permits. See PRECAUTIONS.

HOW SUPPLIED

Ringer’s Irrigation USP is supplied sterile and nonpyrogenic in PIC™ (Plastic Irrigation Containers). The 1000 mL containers are packaged 16 per case.

NDC | Cat. No. | Size
Ringer’s Irrigation USP
0264-2202-00 | R5310-01 | 1000 mL

STORAGE AND HANDLING

Exposure of pharmaceutical products to heat should be minimized. Avoid excessive heat. Protect from freezing. Store at 20°C to 25°C (68°F to 77°F); excursions permitted between 15°C to 30°C (59°F to 86°F). [See USP Controlled Room Temperature.] However, brief exposure up to 40°C does not adversely affect the product.

Do not warm above 150°F (66°C).

Revised: June 2023

PIC is a trademark of B. Braun Medical Inc.

Directions for Use of PIC™ (Plastic Irrigation Container)

Not for injection.

Aseptic technique is required.

1. Caution – Before use, perform the following checks:

(a) Read the label. Ensure solution is the one ordered and is within the expiration date.

(b) Invert container and inspect the solution in good light for cloudiness, haze, or particulate matter; check the container for leakage or damage. Any container which is suspect should not be used.

Use only if solution is clear and container and seal are intact.

Single-dose container. Discard unused portion.

2. Outer Closure Removal – Grasp the container with one hand and turn the breakaway ring counterclockwise with the other hand until slight resistance is felt. Then, twisting the container in the opposite direction, turn the breakaway ring sharply until the entire outer cap is loose and can be lifted off. (Figure 1)

3. Connect the administration set through the sterile set port according to set instructions (Figure 2) or remove screw cap and pour.

4. Do not warm above 150°F (66°C) to assure minimal bottle distortion. Keep bottles upright.

B. Braun Medical Inc.
Bethlehem, PA 18018-3524 USA

1-800-227-2862

Y36-003-073 LD-767-1

PRINCIPAL DISPLAY PANEL - 1000 mL Bottle Label

Ringer’s Irrigation USP

Isotonic Solution for Irrigation

REF R5310-01

NDC 0264-2202-00

1000 mL
PIC™ Container

Rx only

Lot

Exp.

Each 100 mL contains:
Sodium Chloride USP 0.86 g
Potassium Chloride USP 0.03 g
Calcium Chloride•2H2O USP 0.033 g
Water for Injection USP qs
Contains no bacteriostat.

pH: 5.8 (5.0-7.5)
310 mOsmol/liter (calc.)

Electrolytes (mEq/liter):
Na^+147 K^+4 Ca^++ 4.5 Cl^– 156

Sterile, nonpyrogenic. Single-dose container. Discard unused portion.

Not for Injection. Use only if solution is clear and container and seal are intact.

Warning: Do not warm above 150°F (66°C).

Store at 20°C to 25°C (68°F to 77°F). [See USP Controlled Room Temperature.] Avoid excessive heat. Protect from freezing.

Dosage: See Prescribing Information.

Not made with natural rubber latex, PVC or DEHP.

B. Braun Medical Inc.
Bethlehem, PA 18018-3524 USA
1-800-227-2862

Y37-002-589 LD-768-1

Ringer’s Irrigation USP